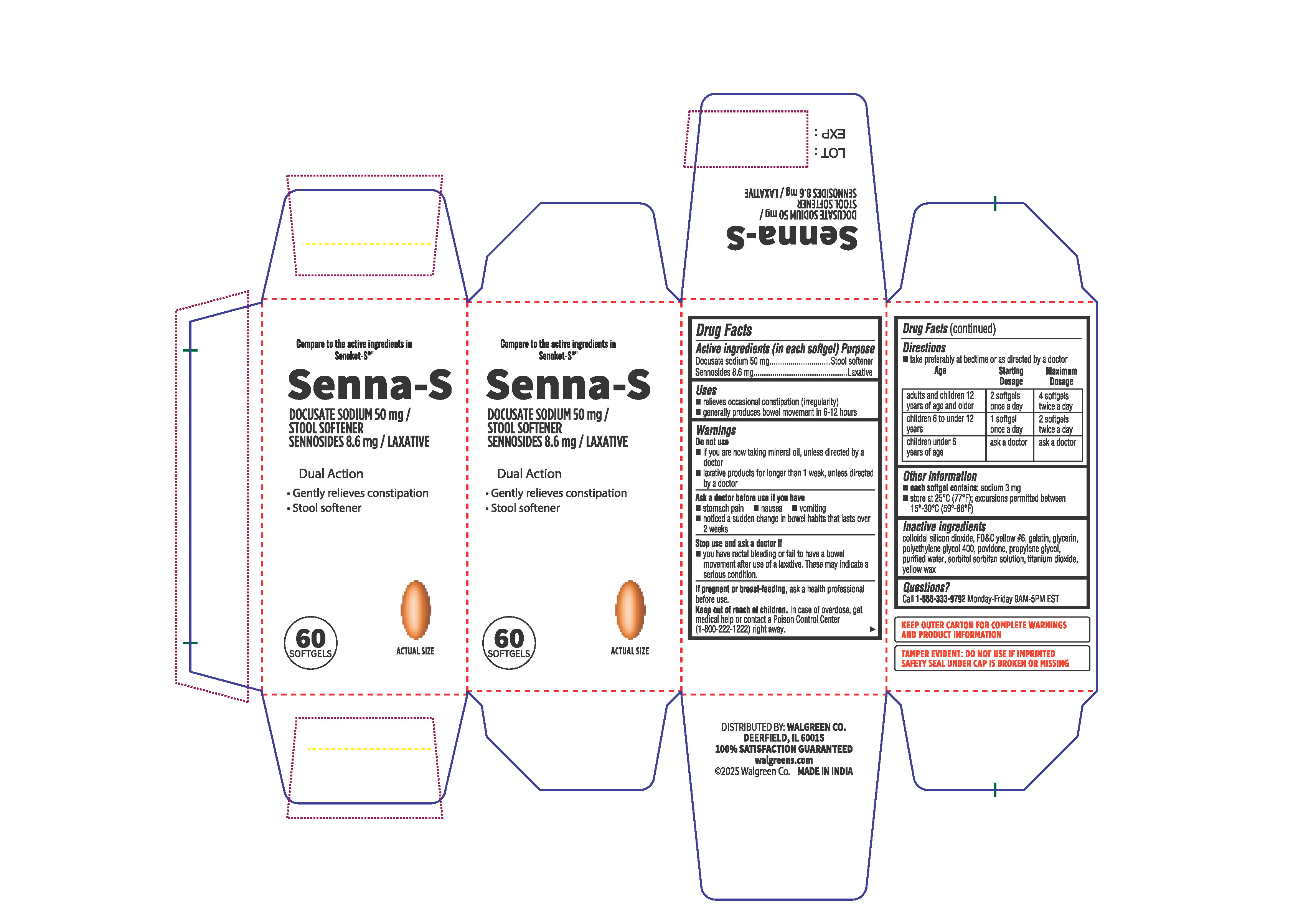 DRUG LABEL: Senna-S
NDC: 0363-6683 | Form: CAPSULE, LIQUID FILLED
Manufacturer: Walgreens
Category: otc | Type: HUMAN OTC DRUG LABEL
Date: 20251231

ACTIVE INGREDIENTS: SENNOSIDES 8.6 mg/1 1; DOCUSATE SODIUM 50 mg/1 1
INACTIVE INGREDIENTS: SILICON DIOXIDE; SORBITOL; GLYCERIN; POVIDONE; YELLOW WAX; GELATIN; POLYETHYLENE GLYCOL 400; PROPYLENE GLYCOL; WATER; TITANIUM DIOXIDE; FD&C YELLOW NO. 6

SENNA-S

Active Ingredient (in each softgel)

Docusate sodium 50 mg

Sennosides 8.6 mg

Purpose

Stool softener

Laxative

Uses

- relieves occasional constipation (irregularity)
- generally produces bowel movement in 6-12 hours

Warnings Do not use

- if you are now taking mineral oil, unless directed by a doctor
- laxative products for longer than 1 week, unless directed by a doctor

Ask a Doctor before use if you have

- stomach pain
- nausea
- vomiting
- noticed a sudden change in bowel habits that lasts over 2 weeks

Stop use and ask a doctor if

- you have rectal bleeding or fail to have a bowel movement after use of a laxative. These may indicate a serious condition.

If pregnant or breast-feeding,

ask a health professional before use.

Keep out of reach of children.

In case of overdose, get medical help or contact a Poison Control Center (1-800-222-1222) right away.

Directions

- take preferably at bedtime or as directed by a doctor

age | starting dosage | maximum dosage
adults and children 12 years of age and older | 2 softgels once a day | 4 softgels twice a day
children 6 to under 12 years | 1 softgel once a day | 2 softgels twice a day
children under 6 years of age | ask a doctor | ask a doctor

Other Information

- each softgel contains: sodium 3 mg
- store at 25°C (77°F); excursions permitted between 15°- 30°C (59°- 86°F)

Inactive Ingredients

colloidal silicon dioxide, FD&C yellow # 6, gelatin, glycerin, polyethylene glycol 400, povidone, propylene glycol, purified water,sorbitol sorbitan solution, titanium dioxide, yellow wax.

Questions?

Call 1-888-333-9792 Monday - Friday 9AM-5PM EST